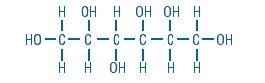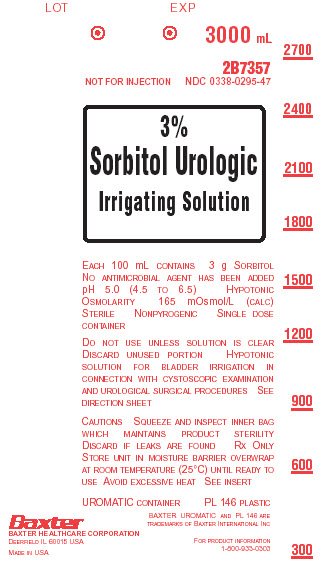 DRUG LABEL: Sorbitol
NDC: 0338-0295 | Form: IRRIGANT
Manufacturer: Baxter Healthcare Corporation
Category: prescription | Type: HUMAN PRESCRIPTION DRUG LABEL
Date: 20191231

ACTIVE INGREDIENTS: SORBITOL 30.00 g/1000.00 mL
INACTIVE INGREDIENTS: WATER

3% Sorbitol Urologic Irrigating Solution
in UROMATIC Plastic Container

DESCRIPTION

3% Sorbitol Urologic Irrigating Solution is a sterile, nonpyrogenic, nonhemolytic, electrically nonconductive solution in a single dose UROMATIC Plastic Container for use as a urologic irrigating solution. Each liter contains 30 g Sorbitol in Water for Injection. pH 5.0 (4.5 to 6.5). Osmolarity 165 mOsmol/L (calc.). No antimicrobial agent has been added.

Sorbitol is a reduced form of dextrose and is designated chemically as D-Glucitol,

The UROMATIC plastic container is fabricated from a specially formulated polyvinyl chloride (PL 146 plastic). The amount of water that can permeate from inside the container into the overwrap is insufficient to affect the solution significantly. Solutions in contact with the plastic container can leach out certain of its chemical components in very small amounts within the expiration period, e.g., di-2-ethylhexyl phthalate (DEHP), up to 5 parts per million; however, the safety of the plastic has been confirmed in tests in animals according to USP biological tests for plastic containers as well as by tissue culture toxicity studies.

CLINICAL PHARMACOLOGY

3% Sorbitol Urologic Irrigating Solution is useful as an irrigating fluid for the urinary bladder because the sorbitol solution is nonhemolytic, electrically nonconductive, and provides a high degree of visibility for urologic procedures requiring endoscopy. During transurethral surgical procedures, the solution acts as a lavage for removing blood and tissue fragments. It is also useful as an irrigating fluid to maintain the patency of an indwelling catheter in the immediate postoperative period. If absorbed either intravascularly or extravascularly during transurethral resections, the sorbitol will be either metabolized to carbon dioxide and water via the fructose pathway, or excreted by a normally functioning kidney.

INDICATIONS AND USAGE

3% Sorbitol Urologic Irrigating Solution is indicated for use as a urologic irrigating fluid with endoscopic instruments during transurethral procedures requiring distension, irrigation, and lavage of the urinary bladder. It may be used for lavage of an indwelling catheter to maintain patency.

CONTRAINDICATIONS

Anuria.

WARNINGS

Not for injection.

Not for use in patients with documented or suspected fructose intolerance.

Solutions for urologic irrigation must be used with caution in patients with severe cardiopulmonary or renal dysfunction.

Irrigating fluids used during transurethral prostatectomy have been demonstrated to enter the systemic circulation in relatively large volumes; thus sorbitol irrigating solution must be regarded as a systemic drug. Absorption of large amounts of fluids containing sorbitol may significantly alter cardiopulmonary and renal dynamics. Appropriate patient monitoring should be maintained due to the possibility of fluid overload. Should fluid overload occur, intensive fluid and electrolyte management is necessary. Monitoring of fluid and electrolyte levels beyond the acute phase may be considered due to the possibility of delayed fluid absorption. (See ADVERSE REACTIONS, Post-Marketing Experience)

Hyperglycemia from metabolism of absorbed sorbitol may occur in patients with diabetes mellitus.

The contents of an opened container should be used promptly to minimize the possibility of bacterial growth or pyrogen formation. Discard the unused portion of irrigating solution since no antimicrobial agent has been added.

PRECAUTIONS

The cardiovascular status, especially of the patient with cardiac disease, should be carefully observed before and during transurethral resection of the prostate when using 3% Sorbitol Urologic Irrigating Solution, because the quantity of fluid absorbed into the systemic circulation by opened prostatic veins may produce significant expansion of the intravascular fluid and lead to fulminating congestive heart failure.

Shift of sodium free intracellular fluid into the extracellular compartment, following systemic absorption may lower serum concentration and aggravate preexisting hyponatremia.

Excessive loss of water and electrolytes may lead to serious imbalances. With continuous administration of solution, loss of water may occur in excess of electrolytes, producing hypernatremia.

Sustained diuresis that results from transurethral irrigation with sorbitol irrigating solutions may obscure and intensify inadequate hydration or hypovolemia.

Pregnancy

Teratogenic Effects

Animal reproduction studies have not been conducted with 3% Sorbitol Urologic Irrigating Solution. It is not known whether 3% Sorbitol Urologic Irrigating Solution can cause fetal harm when administered to a pregnant woman or can affect reproductive capacity. 3% Sorbitol Urologic Irrigating Solution should be given to a pregnant woman only if clearly needed.

Pediatric Use

Safety and effectiveness in pediatric patients have not been established.

Geriatric Use

Clinical studies of Irrigation Solutions did not include sufficient numbers of subjects aged 65 and over to determine whether they respond differently from other younger subjects. Other reported clinical experience has not identified differences in responses between the elderly and younger patients.

Do not administer unless the solution is clear and the seal is intact.

ADVERSE REACTIONS

Life threatening adverse reactions with intravenous sorbitol infusions have been reported in patients with fructose intolerance.

The literature reports occasional adverse reactions for intravenous sorbitol infusions. These include disturbances such as acidosis, electrolyte loss, marked diuresis, urinary retention, edema, dryness of mouth and thirst, and dehydration; cardiovascular/pulmonary disorders such as pulmonary congestion, hypotension, tachycardia, angina-like pains, and other general reactions such as blurred vision, convulsions, nausea, vomiting, diarrhea, rhinitis, chills, vertigo, and backache. Allergic reactions reported to occur from sorbitol include urticaria.

Should adverse reactions occur, discontinue the irrigant and reevaluate the clinical status of the patient.

Post-Marketing Experience

Following off-label use of 3% Sorbitol Urologic Irrigating Solution for hysteroscopic procedures in women, life-threatening adverse events related to fluid overload have been reported.

DOSAGE AND ADMINISTRATION

The volume of solution needed will vary with the nature and duration of the urologic procedure.

If desired, warm in overwrap to near body temperature in a water bath or oven heated to not more than 45°C.

Parenteral drug products should be inspected visually for particulate matter and discoloration prior to administration whenever solution and container permit.

HOW SUPPLIED

3% Sorbitol Urologic Irrigating Solution in UROMATIC plastic containers is available as follows:

2B7357 | 3000mL | NDC 0338-0295-47

Exposure of pharmaceutical products to heat should be minimized. Avoid excessive heat. It is recommended the product be stored at room temperature (25°C); brief exposure up to 40°C does not adversely affect the product.

DIRECTIONS FOR USE

Tear overwrap down side at slit and remove solution container. Visually inspect the container. If the outlet port protector is damaged, detached, or not present, discard container as solution path sterility may be impaired. Some opacity of the plastic due to moisture absorption during the sterilization process may be observed. This is normal and does not affect the solution quality or safety. The opacity will diminish gradually. Check for minute leaks by squeezing bag firmly. If leaks are found, discard solution as sterility may be impaired.

Use Aseptic Technique.

1. Suspend container using hanger hole.
2. Remove protector from outlet port.
3. Attach irrigation set. Refer to complete directions accompanying set.

Baxter Healthcare Corporation
Deerfield, IL 60015 USA

Printed in USA

Baxter and Uromatic are trademarks of Baxter International Inc.

07-19-00-0227
Rev. January 2018

PRINCIPAL DISPLAY PANEL - PACKAGING LABELING

Container Label

Container Label

LOT
EXP

3000 mL

2B7357
NDC 0338-0295-47

NOT FOR INJECTION

3%
Sorbitol Urologic
Irrigating Solution

EACH 100 mL CONTAINS 3 g SORBITOL
NO ANTIMICROBIAL AGENT HAS BEEN ADDED
pH 5.0 (4.5 TO 6.5) HYPOTONIC
OSMOLARITY 165 mOsmol/L (CALC)
STERILE NONPYROGENIC SINGLE DOSE
CONTAINER

DO NOT USE UNLESS SOLUTION IS CLEAR
DISCARD UNUSED PORTION HYPOTONIC
SOLUTION FOR BLADDER IRRIGATION IN
CONNECTION WITH CYSTOSCOPIC EXAMINATION
AND UROLOGICAL SURGICAL PROCEDURES SEE
DIRECTION SHEET

CAUTIONS SQUEEZE AND INSPECT INNER BAG
WHICH MAINTAINS PRODUCT STERILITY
DISCARD IF LEAKS ARE FOUND RX ONLY
STORE UNIT IN MOISTURE BARRIER OVERWRAP
AT ROOM TEMPERATURE (25°C) UNTIL READY TO
USE AVOID EXCESSIVE HEAT SEE INSERT

UROMATIC CONTAINER

PL 146 PLASTIC

BAXTER UROMATIC AND PL 146 ARE
TRADEMARKS OF BAXTER INTERNATIONAL INC

Baxter Logo
BAXTER HEALTHCARE CORPORATION
DEERFIELD IL 60015 USA

MADE IN USA

FOR PRODUCT INFORMATION
1-800-933-0303